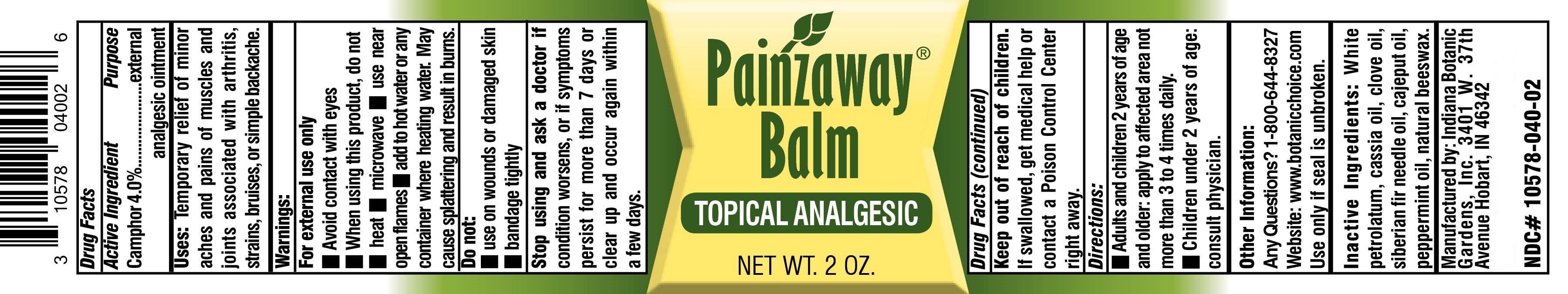 DRUG LABEL: Painzaway Balm
NDC: 10578-040 | Form: OINTMENT
Manufacturer: Indiana Botanic Gardens
Category: otc | Type: HUMAN OTC DRUG LABEL
Date: 20151028

ACTIVE INGREDIENTS: CAMPHOR (SYNTHETIC) 4 g/100 g
INACTIVE INGREDIENTS: PETROLATUM; ABIES SIBIRICA LEAF OIL; CAJUPUT OIL; CHINESE CINNAMON OIL; CLOVE LEAF OIL; PEPPERMINT OIL; YELLOW WAX

Painzaway Balm

Active Ingredient

Camphor 4.0%

Purpose

external analgesic ointment

Uses:

Temporary relief of minor aches and pains of muscles and joints associated with arthritis, strains, bruises or simple backache.

Warnings

For external use only.

Avoid contact with the eyes.

When using this product, do not:

heat

microwave

use near open flames

add to hot water or any container where heating water.

May cause splattering and result in burns.

Do Not

use on wounds or damaged skin

bandage tightly

Stop using and ask a doctor if

condition worsens, or if symptoms persist for more than 7 days or clear up and occur again within a few days.

Keep out of reach of children. If swallowed, get medical help or contact a Poison Control Center right away.

Directions

Adults and children 2 years of age and older: apply to affected area not more than 3 to 4 times daily.

Children under 2 years of age: consult physician.

Other information

Any Questions? 1-800-644-8327

website: www.botanicchoice.com

Use only if seal is unbroken.

Inactive ingredients

White petrolatum, cassia oil, clove oil, siberian fir needle oil, cajeput oil, peppermint oil, natural beeswax.

Manufactured by: Indiana Botanic Gardens, Inc.

3401 W. 37th Avenue Hobart, IN 46342

PACKAGE LABEL

Painzaway Balm

Topical Analgesic

Net Wt. 2oz.